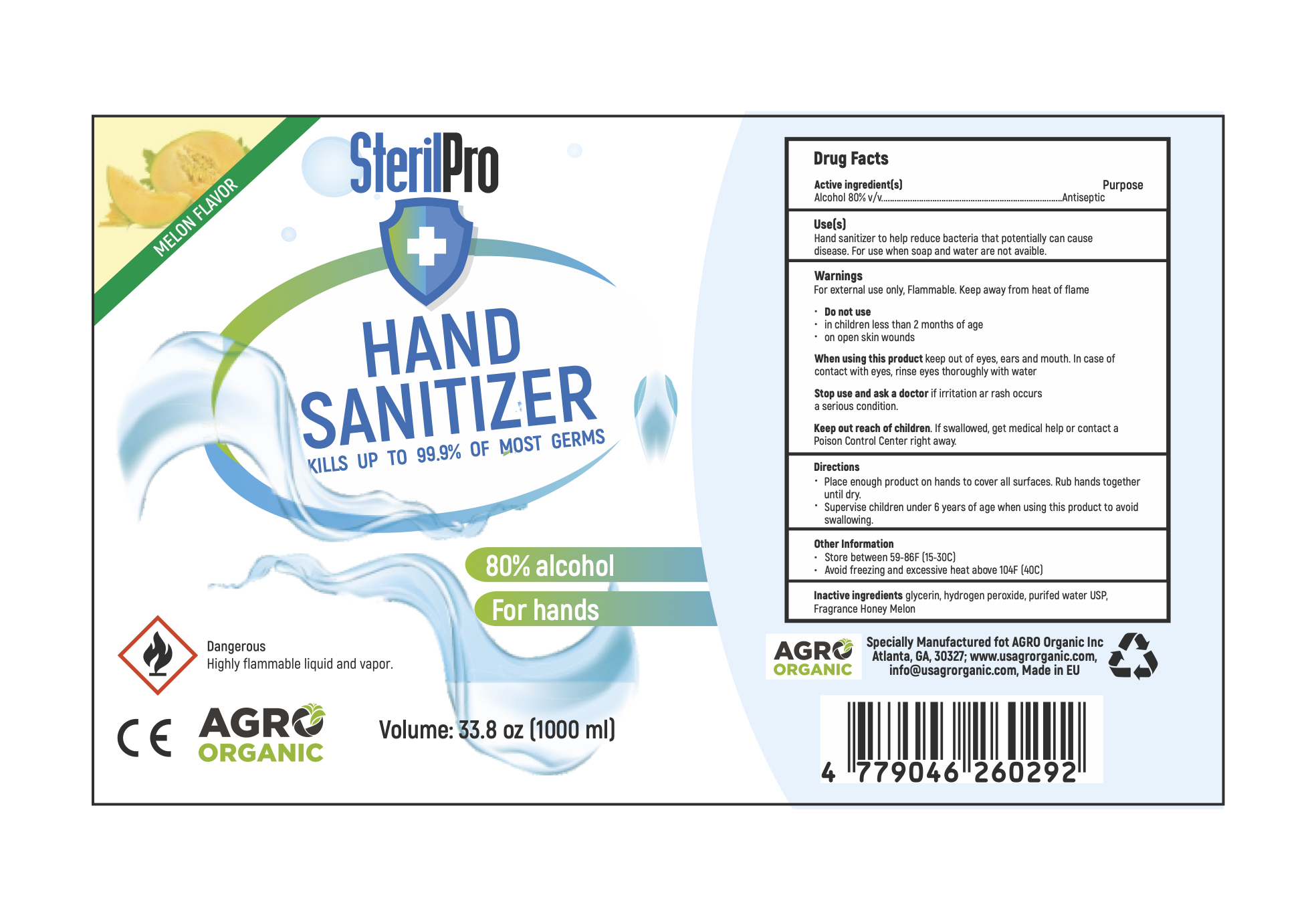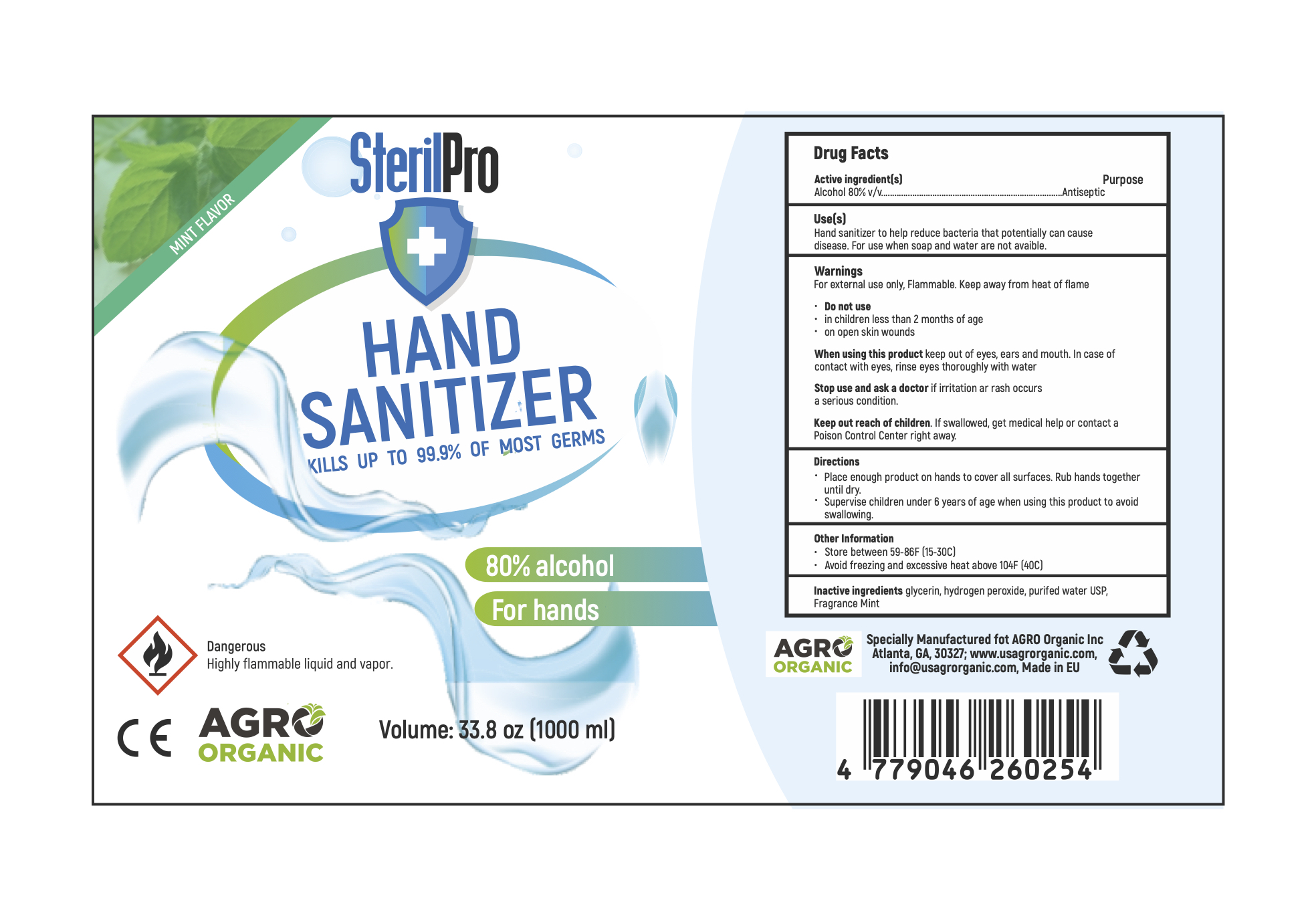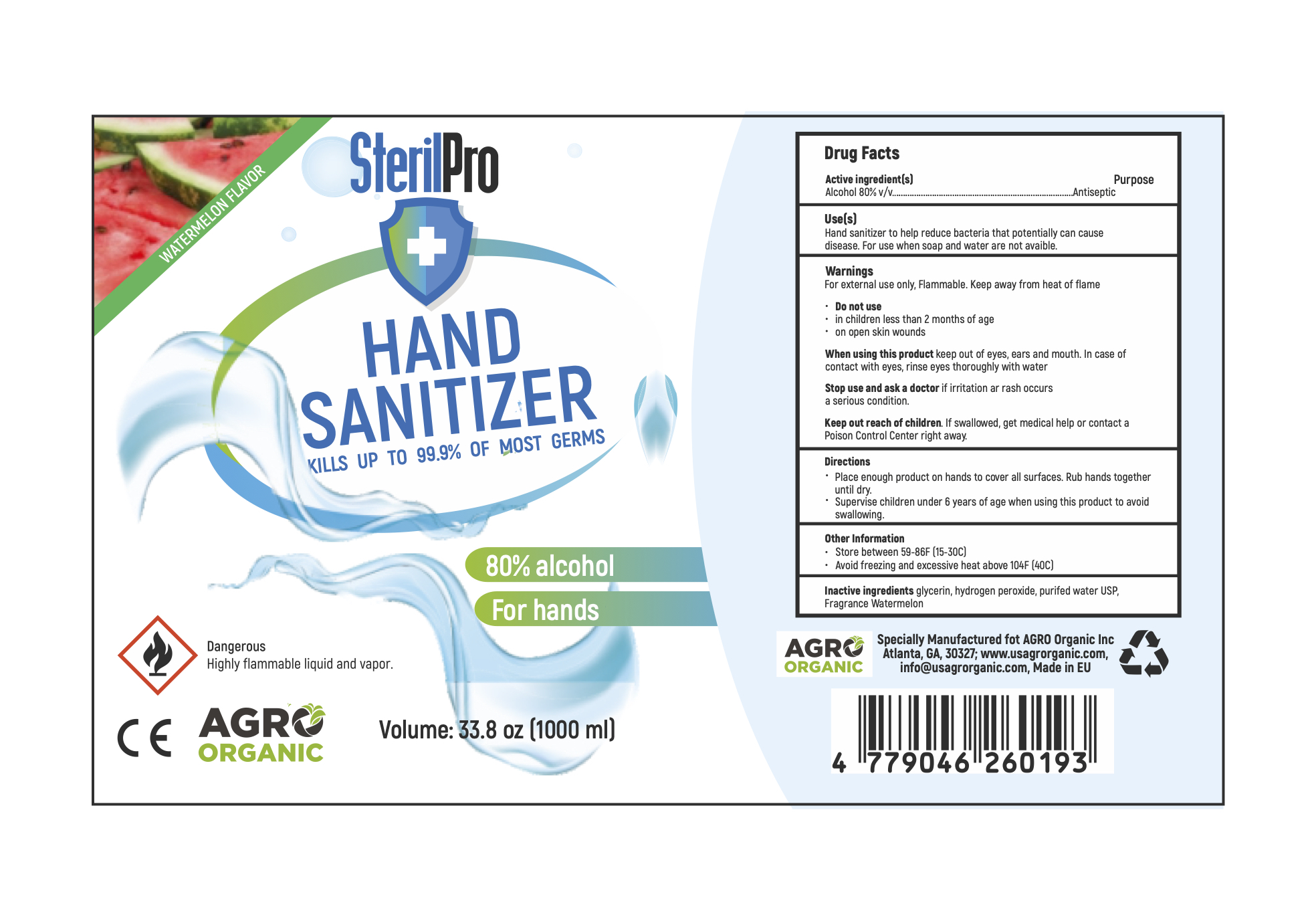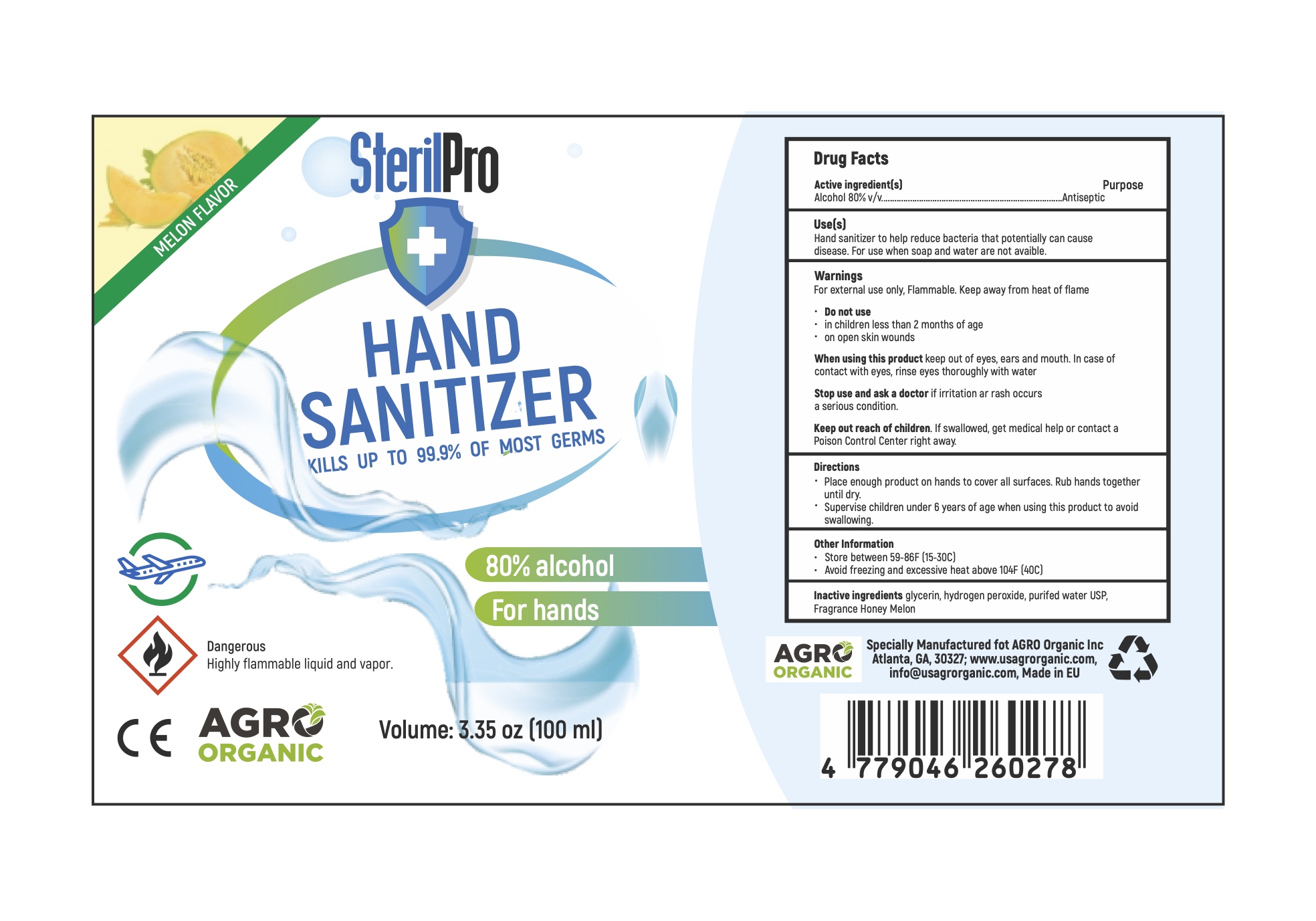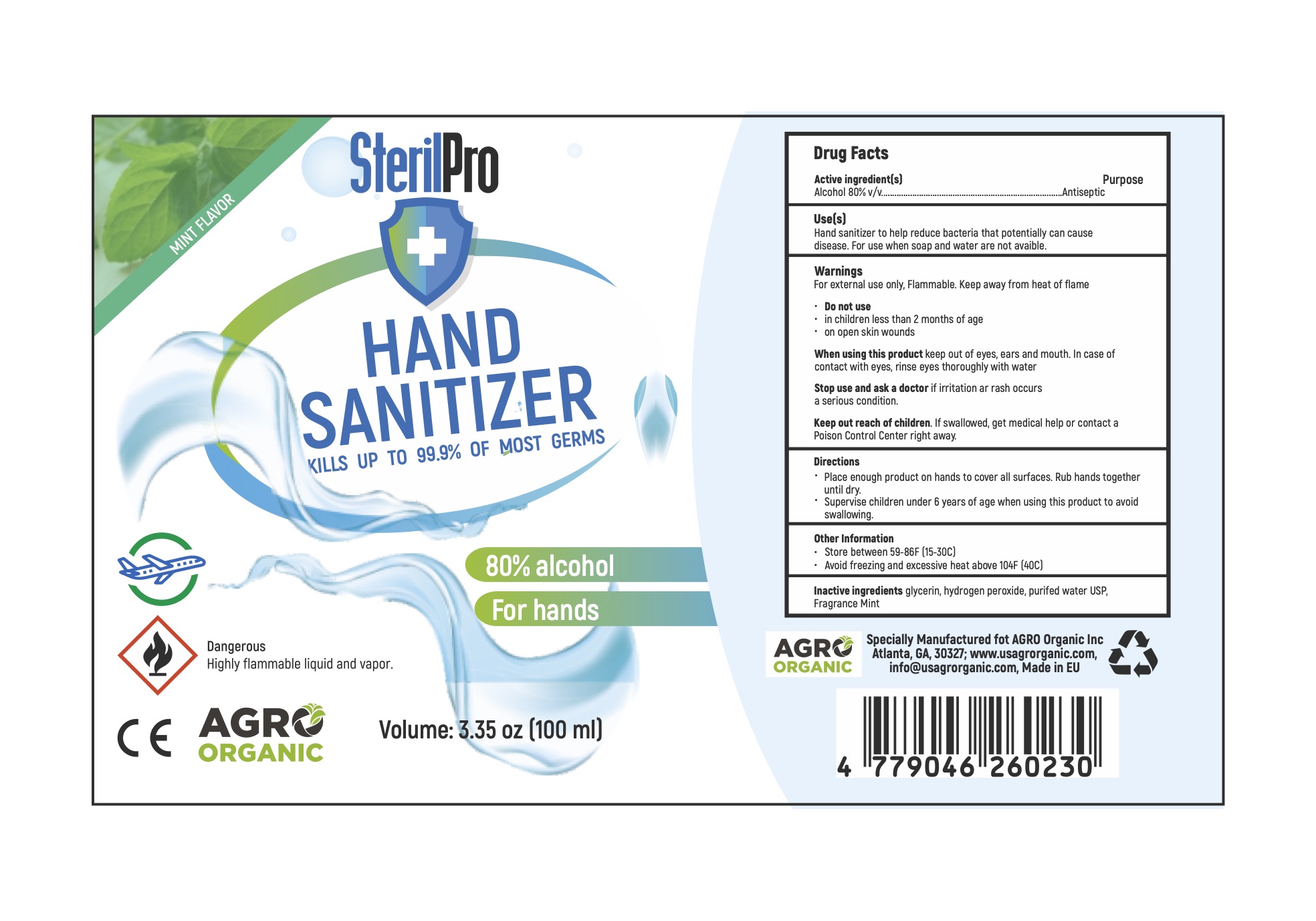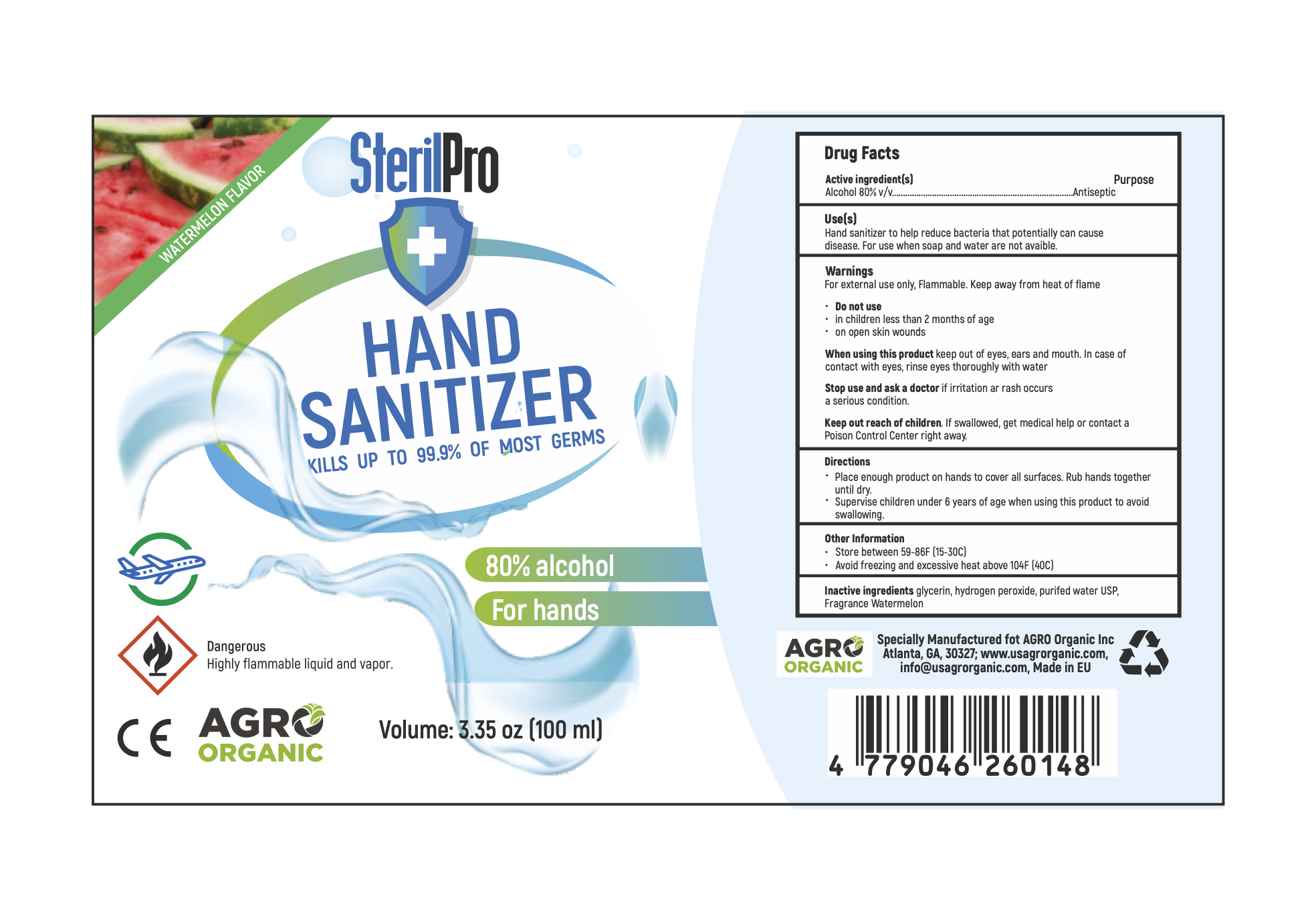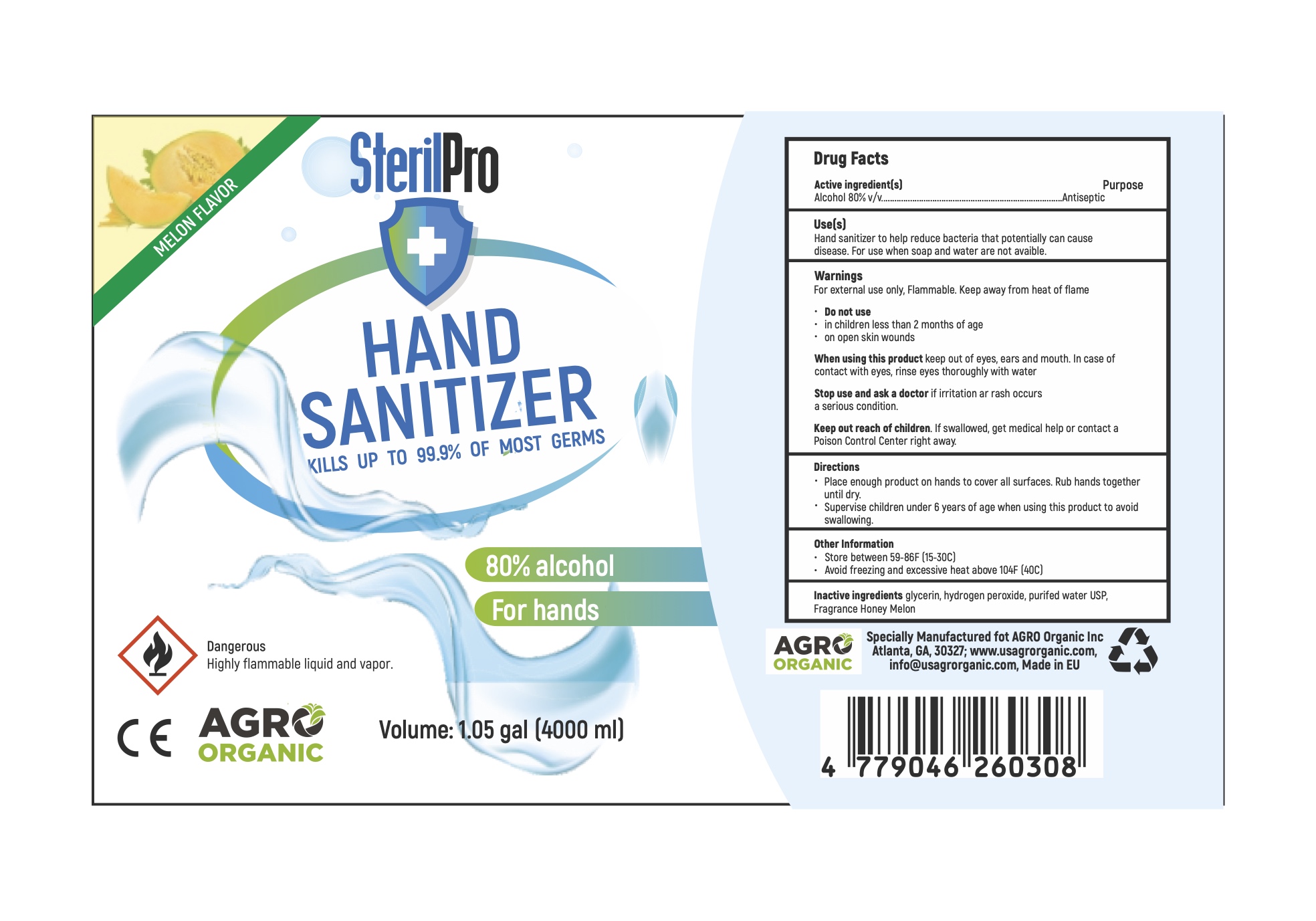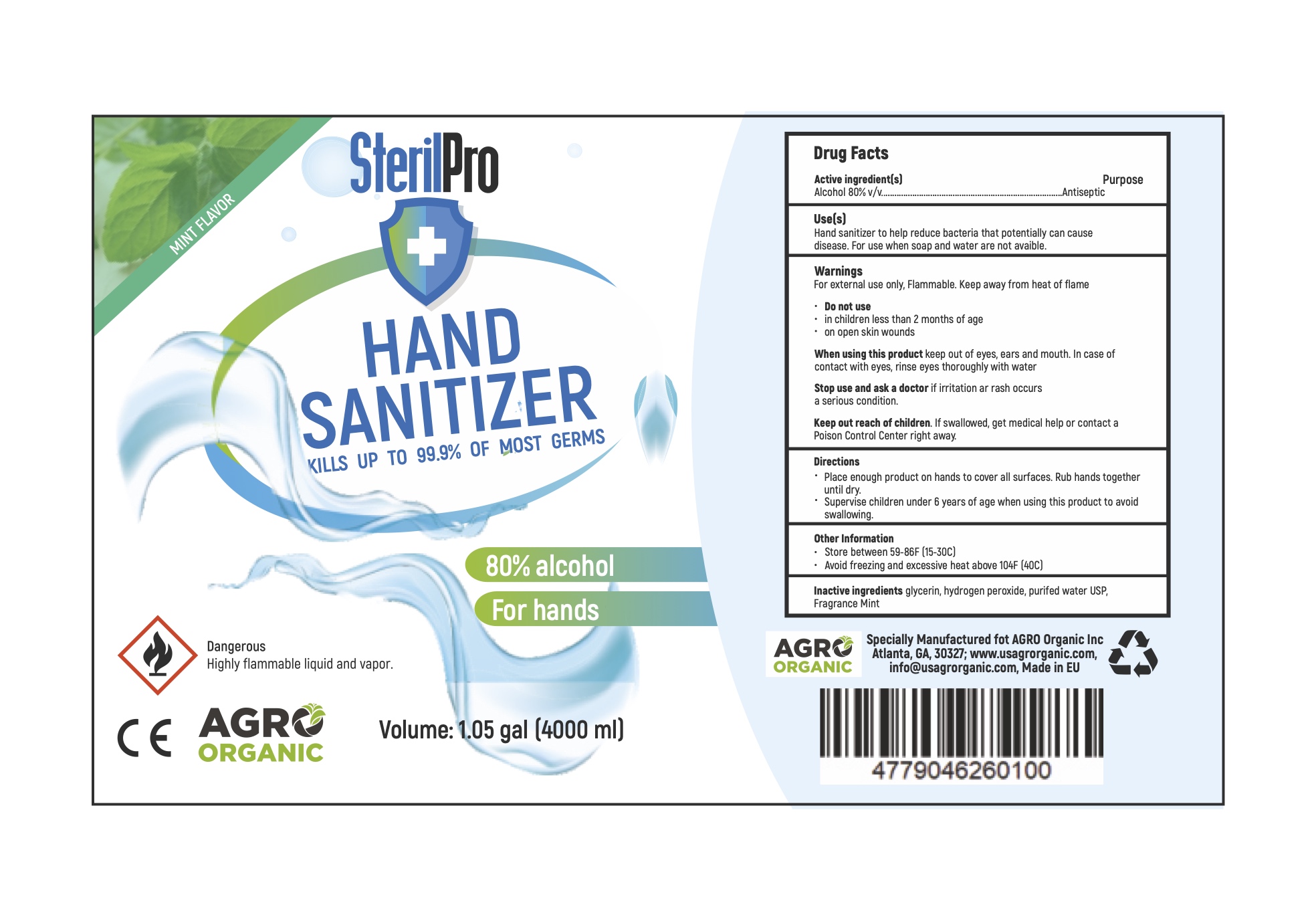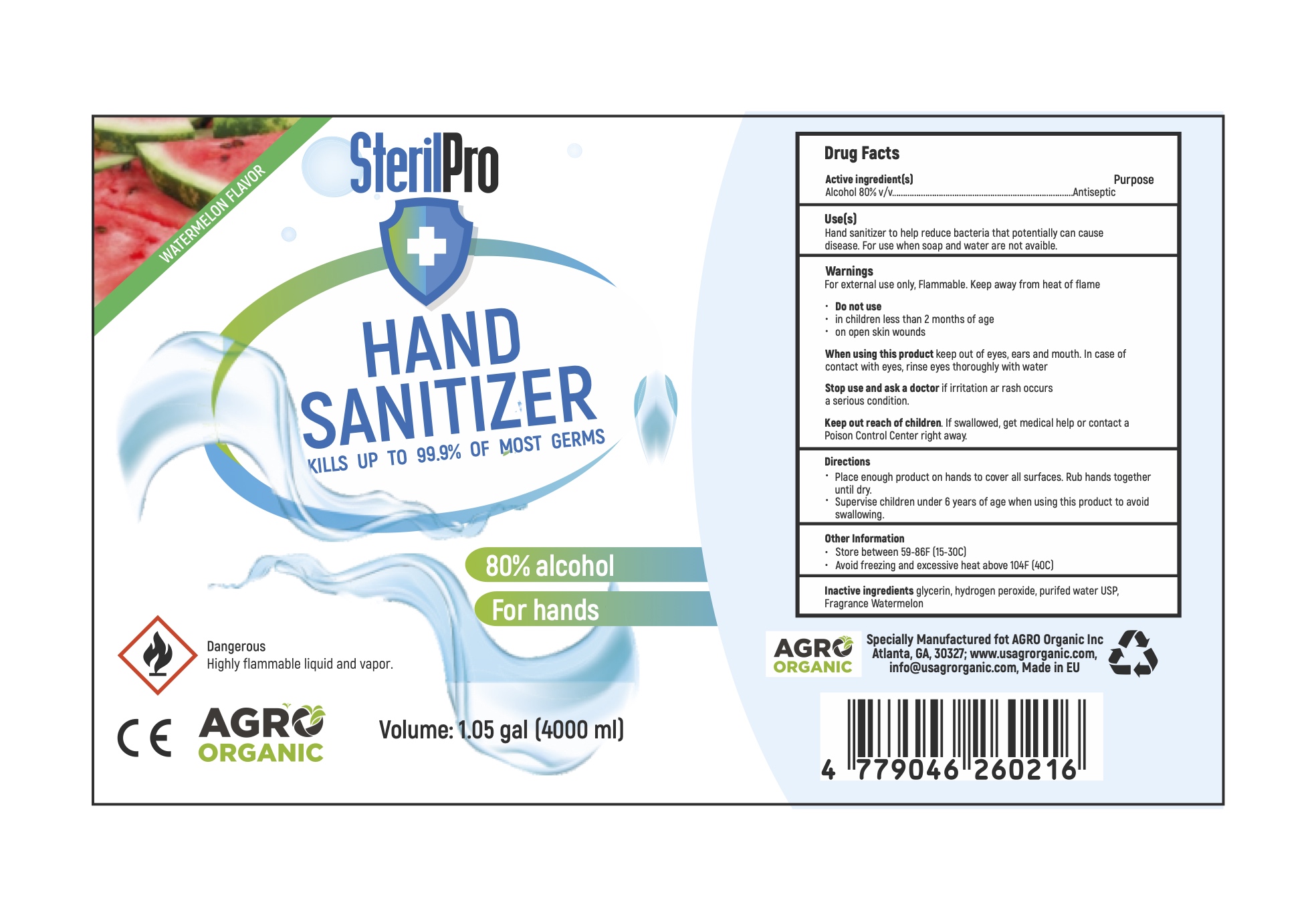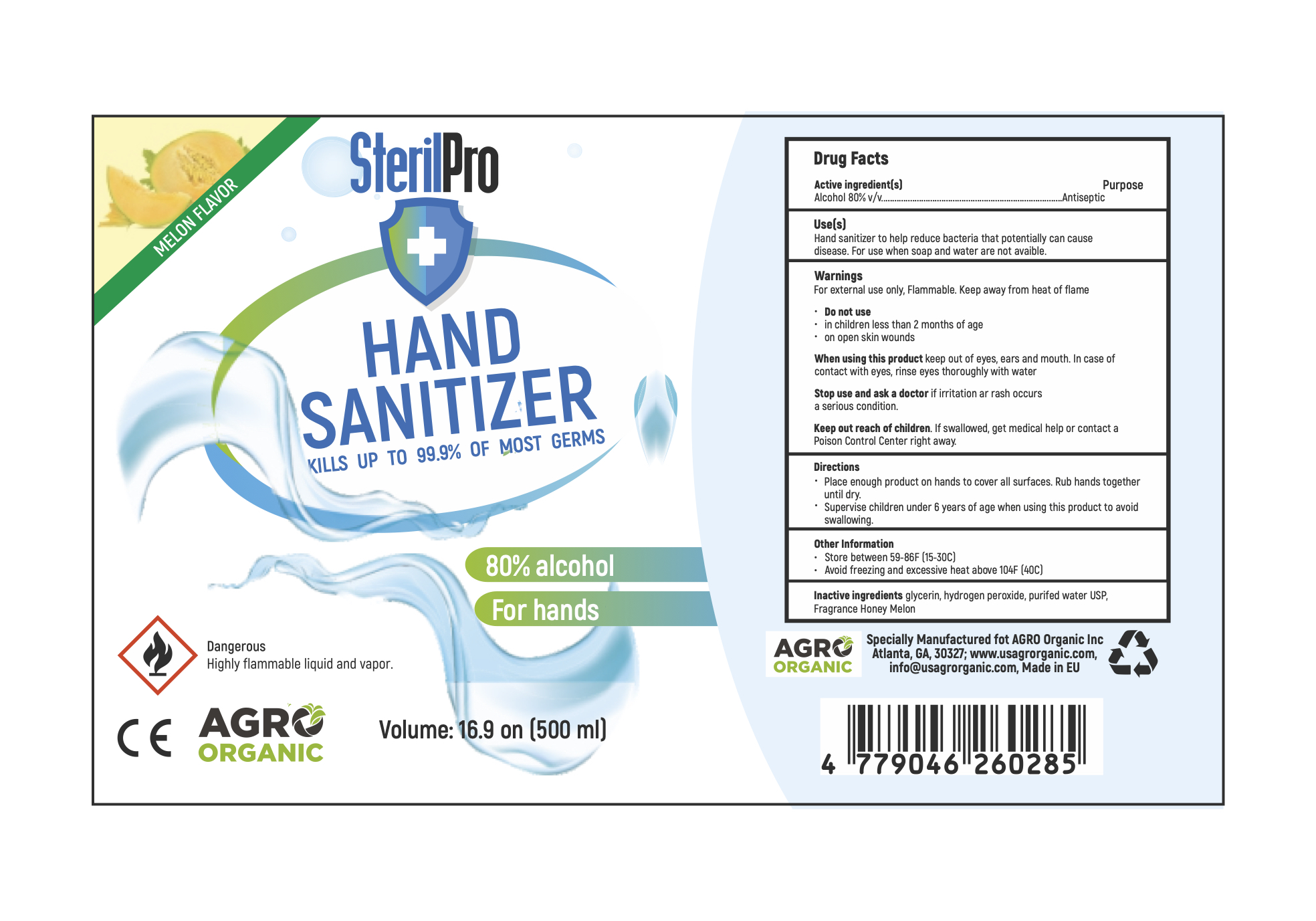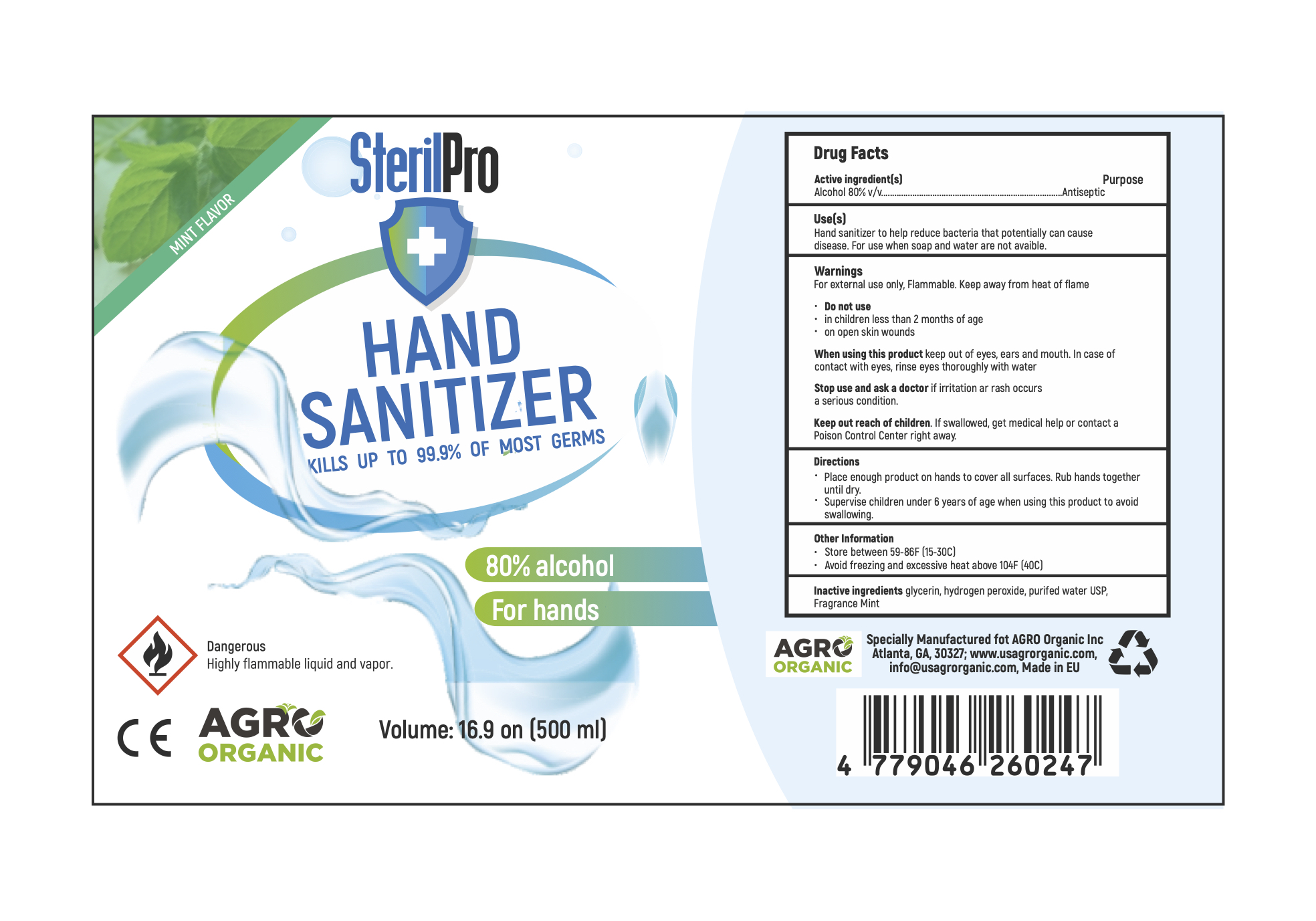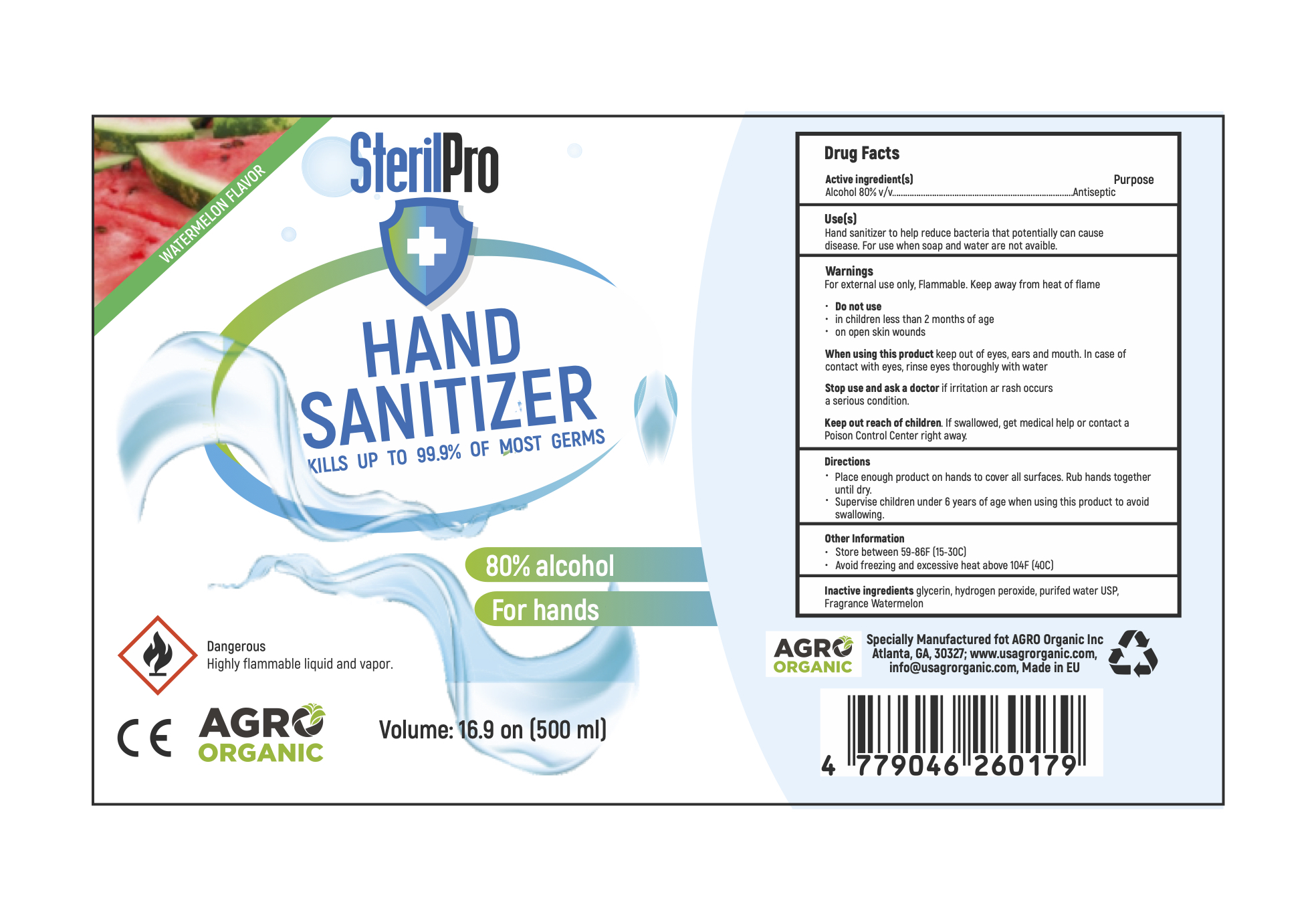 DRUG LABEL: Hand Sanitizer
NDC: 78897-003 | Form: LIQUID
Manufacturer: Agroorganika UAB
Category: otc | Type: HUMAN OTC DRUG LABEL
Date: 20200727

ACTIVE INGREDIENTS: ALCOHOL 80 mL/100 mL
INACTIVE INGREDIENTS: GLYCERIN 1.45 mL/100 mL; HYDROGEN PEROXIDE 0.125 mL/100 mL; WATER

Active Ingredient(s)

Alcohol 80% v/v. Purpose: Antiseptic

Purpose

Antiseptic, Hand Sanitizer

Use

Hand Sanitizer to help reduce bacteria that potentially can cause disease. For use when soap and water are not available.

Warnings

For external use only. Flammable. Keep away from heat or flame

Do not use

- in children less than 2 months of age
- on open skin wounds

When using this product keep out of eyes, ears, and mouth. In case of contact with eyes, rinse eyes thoroughly with water.
Stop use and ask a doctor if irritation or rash occurs. These may be signs of a serious condition.
Keep out of reach of children. If swallowed, get medical help or contact a Poison Control Center right away.

Stop use and ask a doctor if irritation or rash occurs. These may be signs of a serious condition.

Keep out of reach of children. If swallowed, get medical help or contact a Poison Control Center right away.

Directions

- Place enough product on hands to cover all surfaces. Rub hands together until dry.
- Supervise children under 6 years of age when using this product to avoid swallowing.

Inactive ingredients

NDC 78897-001: glycerin, hydrogen peroxide, purified water USP, Fragrance Honey Melon

NDC 78897-002: glycerin, hydrogen peroxide, purified water USP, Fragrance Watermelon

NDC 78897-003: glycerin, hydrogen peroxide, purified water USP, Fragrance Mint

Other information

- Store between 15-30C (59-86F)
- Avoid freezing and excessive heat above 40C (104F)

Package Label - Principal Display Panel

100 mL NDC: 78897-001-01

500 mL NDC: 78897-001-02

1000 mL NDC: 78897-001-03

4000 mL NDC: 78897-001-04

100 mL NDC: 78897-002-01

500 mL NDC: 78897-002-02

1000 mL NDC: 78897-002-03

4000 mL NDC: 78897-002-04

100 mL NDC: 78897-003-01

500 mL NDC: 78897-003-02

1000 mL NDC: 78897-003-03

4000 mL NDC: 78897-003-04